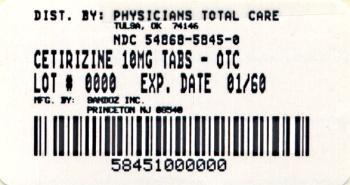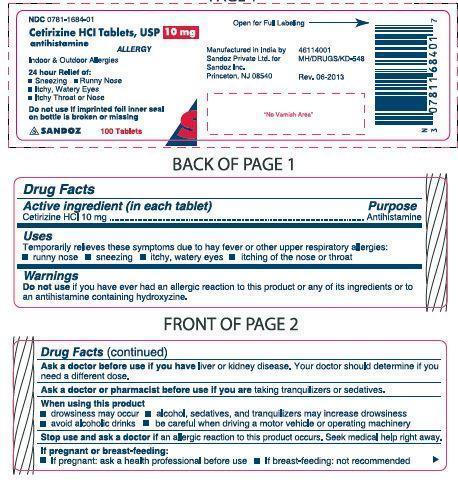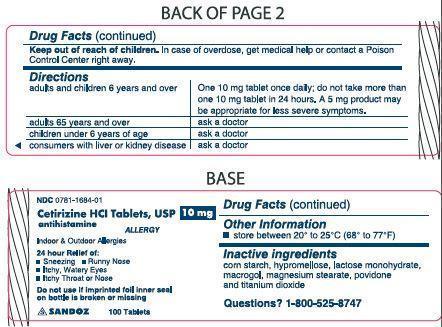 DRUG LABEL: Cetirizine Hydrochloride
NDC: 54868-5845 | Form: TABLET
Manufacturer: Physicians Total Care, Inc.
Category: otc | Type: HUMAN OTC DRUG LABEL
Date: 20150508

ACTIVE INGREDIENTS: CETIRIZINE HYDROCHLORIDE 10 mg/1 1
INACTIVE INGREDIENTS: STARCH, CORN; HYPROMELLOSES; LACTOSE MONOHYDRATE; MAGNESIUM STEARATE; POVIDONES; TITANIUM DIOXIDE; POLYETHYLENE GLYCOLS

Drug Facts

Active ingredient

(in each tablet)

Cetirizine HCl 10 mg

Purpose

Antihistamine

Keep Out of Reach of Children

In case of overdose, get medical help or contact a Poison Control Center right away.

Uses

Temporarily relieves these symptoms due to hay fever or other upper respiratory allergies:

- runny nose
- sneezing
- itchy, watery eyes
- itching of the nose or throat

Warnings

Do not use if you have ever had an allergic reactions to this product or any of its ingredients or to an antihistamine containing hydroxyzine.

Ask a doctor before use if you have liver or kidney disease. Your doctor should determine if you need a different dose.

Ask a doctor or pharmacist before use if you are taking tranquilizers or sedatives.

When using this product

- drowsiness may occur
- avoid alcoholic drinks
- alcohol, sedatives, and tranquilizers may increase drowsiness
- be careful when driving a motor vehicle or operating machinery

Stop use and ask a doctor if an allergic reaction to this product occurs. Seek medical help right away.

If pregnant or breast-feeding:

- if breast-feeding: not recommended
- if pregnant: ask a health professional before use.

Keep out of reach of children. In case of overdose, get medical help or contact a Poison Control Center right away.

Directions

adults and children 6 years and over | One 10 mg tablet once daily; do not take more than one 10 mg tablet in 24 hours. A 5 mg product may be appropriate for less severe symptoms.
adults 65 years and over | ask a doctor
children under 6 years of age | ask a doctor
consumers with liver or kidney disease | ask a doctor

Other information

- Store between 20º to 25º C (68º to 77º F)

Inactive ingredients

Corn starch, hypromellose, lactose monohydrate, macrogol, magnesium stearate, povidone and titanium dioxide.

Questions? 1-800-525-8747

Manufactured in India by Sandoz Private Ltd.,

for Sandoz Inc., Princeton, NJ 08540

Rev.06/2013

Distributed by:

Physicians Total Care, Inc.

Tulsa, OK 74146

Principal Display Panel

NDC 0781-1684-64

Cetirizine HCl Tablets, USP

10 mg

antihistamine

30 Tablets.

Do not use if individual blister unit is open or torn

ALLERGY

Indoor & Outdoor Allergies

24 hour Relief of

- Sneezing
- Runny Nose
- Itchy, Watery Eyes
- Itchy Throat or Nose

PACKAGE LABEL

NDC 54868-5845-0

Cetirizine HCl Tablets, USP

10 mg

antihistamine